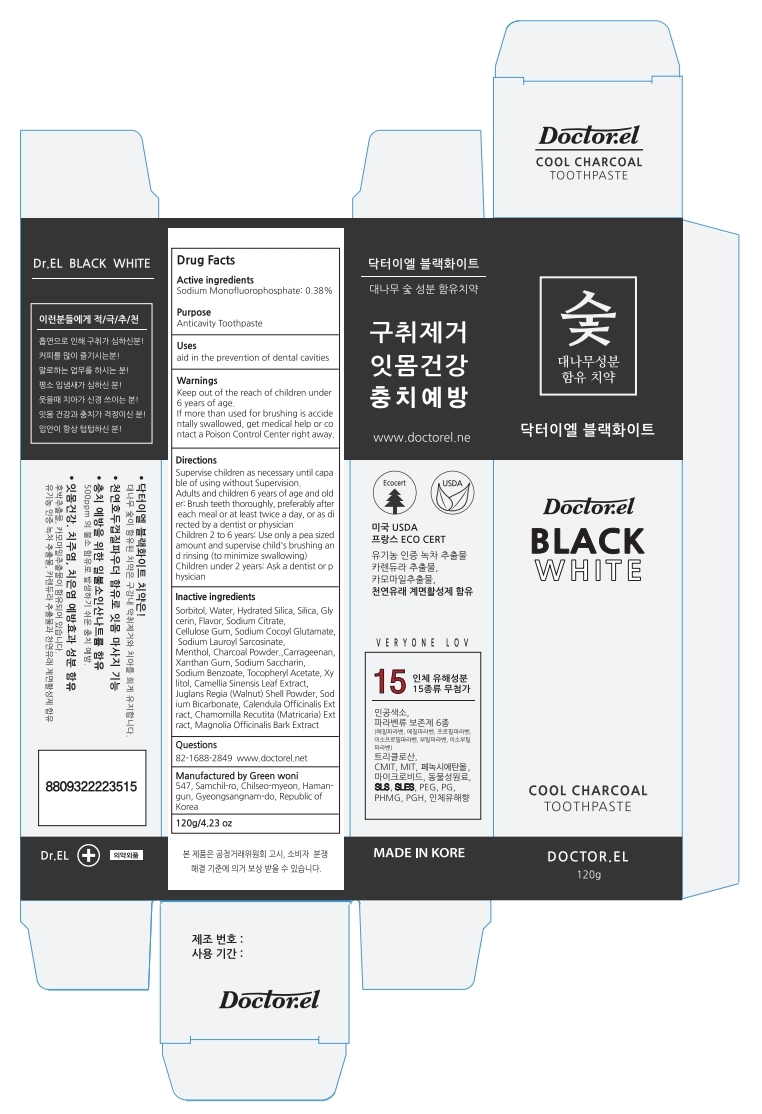 DRUG LABEL: Doctor EL Black White Tooth
NDC: 72440-110 | Form: PASTE, DENTIFRICE
Manufacturer: Dr. EL CO., LTD.
Category: otc | Type: HUMAN OTC DRUG LABEL
Date: 20200702

ACTIVE INGREDIENTS: SODIUM MONOFLUOROPHOSPHATE 0.38 g/100 g
INACTIVE INGREDIENTS: XYLITOL; WATER

ACTIVE INGREDIENT

SODIUM MONOFLUOROPHOSPHATE

PURPOSE

For dental care

Keep out of reach of children

INDICATIONS AND USAGE

Supervise children as necessary until capable of using without Supervision.

Adults and children 6 years of age and older: Brush teeth thoroughly, preferably after each meal or at least twice a day, or as directed by a dentist or physician

Children 2 to 6 years: Use only a pea sized amount and supervise child's brushing and rinsing (to minimize swallowing)

Children under 2 years: Ask a dentist or physician

WARNINGS

Keep out of the reach of children under 6 years of age.

If more than used for brushing is accidentally swallowed, get medical help or contact a Poison Control Center right away.

INACTIVE INGREDIENT

Sorbitol, Water, Hydrated Silica, Silica, Glycerin, Flavor, Sodium Citrate,

Cellulose Gum, Sodium Cocoyl Glutamate, Sodium Lauroyl Sarcosinate,

Menthol, Charcoal Powder.,Carrageenan, Xanthan Gum, Sodium Saccharin,

Sodium Benzoate, Tocopheryl Acetate, Xylitol, Camellia Sinensis Leaf Extract,

Juglans Regia (Walnut) Shell Powder, Sodium Bicarbonate, Calendula Officinalis Extract, Chamomilla Recutita (Matricaria) Extract, Magnolia Officinalis Bark Extract

DOSAGE AND ADMINISTRATION

For dental use only